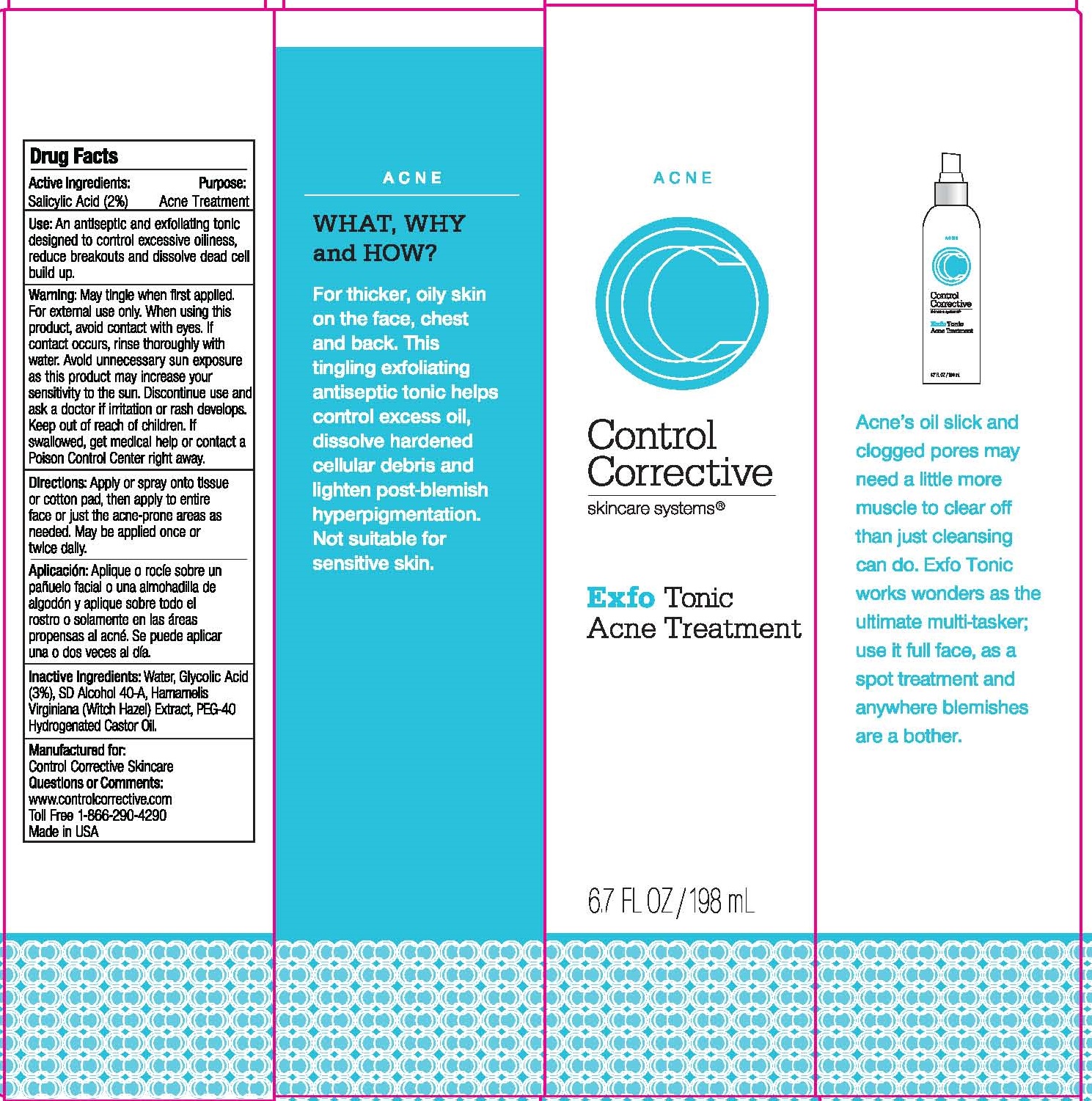 DRUG LABEL: EXFO TONIC ACNE TREATMENT
NDC: 70764-104 | Form: SOLUTION
Manufacturer: CONTROL CORRECTIVE SKINCARE INC
Category: otc | Type: HUMAN OTC DRUG LABEL
Date: 20251231

ACTIVE INGREDIENTS: SALICYLIC ACID 2 g/100 mL
INACTIVE INGREDIENTS: WATER; GLYCOLIC ACID; ALCOHOL; WITCH HAZEL; POLYOXYL 40 HYDROGENATED CASTOR OIL

CONTROL CORRECTIVE - EXFO TONICACNE TREATMENT (70764-104)

ACTIVE INGREDIENTS

SALICYLIC ACID (2.0%)

PURPOSE

ACNE TREATMENT

USE

AN ANTISEPTIC AND EXFOLIATING TONIC DESIGNED TO CONTROL EXCESSIVE OILINESS, REDUCE BREAKOUTS AND DISOLVE DEAD CELL BUILD UP.

WARNINGS

MAY TINGLE WHEN FIRST APPLIED. FOR EXTERNAL USE ONLY. WHEN USING THIS PRODUCT, AVOID CONTACT WITH EYES. IF CONTACT OCCURS, RINSE THOROUGHLY WITH WATER. AVOID UNNECESSARY SUN EXPOSURE AS THIS PRODUCT MAY INCREASE YOUR SENSITIVITY TO THE SUN. DISCONTINUE USE AND ASK A DOCTOR IF IRRITATION OR RASH DEVELOPS.

DIRECTIONS

APPLY OR SPRAY ONTO TISSUE OR COTTON PAD, THEN APPLY TO ENTIRE FACE OR JUST THE ACNE-PRONE AREAS AS NEEDED. MAY BE APPLIED ONCE OR TWICE DAILY.

INACTIVE INGREDIENTS

WATER, GLYCOLIC ACID (3%), SD ALCOHOL 40-A, HAMAMELIS VIRGINIANA (WITCH HAZEL) EXTRACT, PEG-40 HYDROGENATED CASTOR OIL.

KEEP OUT OF REACH OF CHILDREN. IF SWALLOWED, GET MEDICAL HELP OR CONTACT A POISON CONTROL CENTER RIGHT AWAY.

QUESTIONS OR COMMENTS

WWW.CONTROLCORRECTIVE.COM

TOLL FREE 1-866-290-4290

MADE IN USA